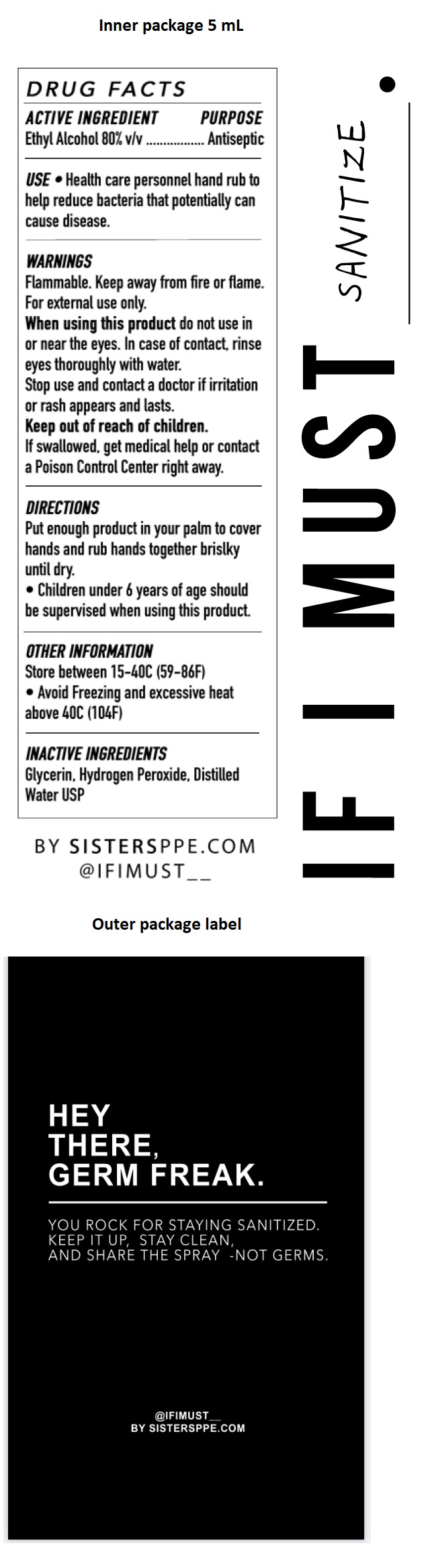 DRUG LABEL: If I Must Sisters PPE Hand Sanitizer
NDC: 80356-050 | Form: LIQUID
Manufacturer: Sisters Personal Protective Equipment, Inc.
Category: otc | Type: HUMAN OTC DRUG LABEL
Date: 20200910

ACTIVE INGREDIENTS: ALCOHOL 80 mL/100 mL
INACTIVE INGREDIENTS: GLYCERIN; HYDROGEN PEROXIDE; WATER

If I Must Sisters PPE Hand Sanitizer

ACTIVE INGREDIENT

Ethyl Alcohol 80% v/v

PURPOSE

Antiseptic

INDICATIONS AND USAGE

USE • Health care personnel hand rub to help reduce bacteria that potentially can cause disease.

WARNINGS

Flammable. Keep away from fire or flame.

For external use only.

When using this product do not use in or near the eyes. In case of contact, rinse eyes thoroughly with water.

Stop use and contact a doctor if irritation or rash appears and lasts.

Keep out of reach of children.

If swallowed, get medical help or contact a Poison Control Center right away.

DIRECTIONS

Put enough product in your palm to cover hands and rub hands together briskly until dry.

• Children under 6 years of age should be supervised when using this product.

OTHER INFORMATION

Store between 15-40C (59-86F)

• Avoid Freezing and excessive heat above 40C (104F)

INACTIVE INGREDIENTS

Glycerin, Hydrogen Peroxide, Distilled Water USP

BY SISTERSPPE.COM

@ IF I MUST_ _

SANITIZE